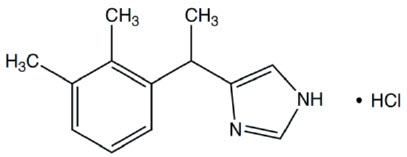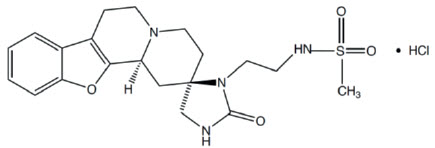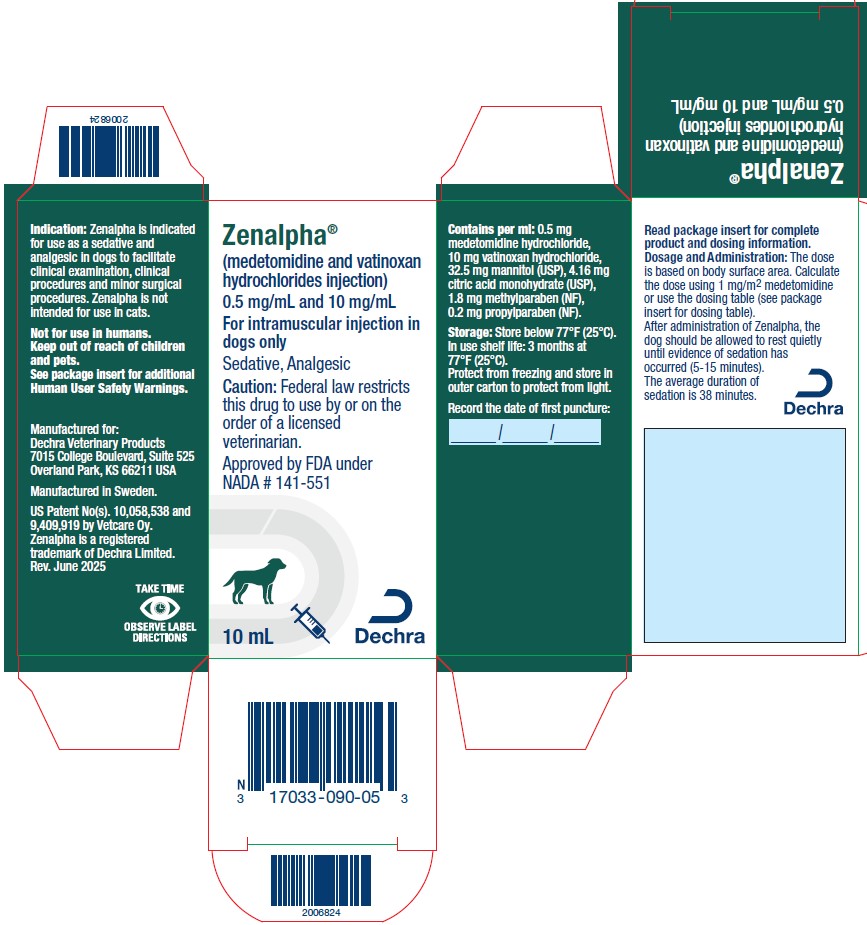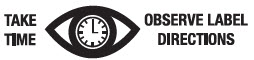 DRUG LABEL: Zenalpha
NDC: 17033-090 | Form: INJECTION, SOLUTION
Manufacturer: Dechra Veterinary Products
Category: animal | Type: PRESCRIPTION ANIMAL DRUG LABEL
Date: 20251219

ACTIVE INGREDIENTS: vatinoxan hydrochloride 10 mg/1 mL; medetomidine hydrochloride 0.5 mg/1 mL

Zenalpha®
(medetomidine and vatinoxan hydrochlorides injection)
0.5 mg/mL and 10 mg/mL

For intramuscular injection in dogs only
Sedative, Analgesic

CAUTION:

Federal law restricts this drug to use by or on the order of a licensed veterinarian.

DESCRIPTION:

Zenalpha is a combination of medetomidine and vatinoxan hydrochlorides. Medetomidine is a racemic mixture containing the active enantiomer, dexmedetomidine, an alpha2-adrenoceptor agonist with sedative and analgesic properties. Vatinoxan is a peripherally selective alpha2-adrenoceptor antagonist, which partially counteracts the cardiovascular depressive effects of dexmedetomidine at peripheral alpha2-adrenoceptors, while preserving the centrally mediated sedative and analgesic effects of dexmedetomidine.

Medetomidine hydrochloride has the chemical name (S,R)-4-[1-(2,3-dimethylphenylethyl)-1H-imidazole hydrochloride. It is a white, crystalline, water soluble substance having a molecular weight of 237 g/mol. The molecular formula is C13H16N2 HCl and the structural formula is:

Vatinoxan hydrochloride has the chemical name N-(2-((2R,12bS)-2'-oxo-1,3,4,6,7,12b-hexahydrospiro[benzofuro[2,3-a] quinolizine-2,4'-imidazolidine]-3'-yl) ethyl) methane sulfonamide hydrochloride. It is a white to pale yellow, crystalline substance, sparingly soluble in water and having a molecular weight of 455 g/mol. The molecular formula is C20 H26 N4 O4 S HCl and the structural formula is:

Each mL of Zenalpha contains 0.5 mg medetomidine hydrochloride, 10 mg vatinoxan hydrochloride, 32.5 mg mannitol (USP), 4.16 mg citric acid monohydrate (USP), 1.8 mg methylparaben (NF), 0.2 mg propylparaben (NF).

INDICATION:

Zenalpha is indicated for use as a sedative and analgesic in dogs to facilitate clinical examination, clinical procedures and minor surgical procedures.

Zenalpha is not intended for use in cats (see Animal Safety Warnings).

DOSAGE AND ADMINISTRATION:

The dose is based on body surface area (BSA). Calculate the dose using 1 mg medetomidine /m^2 BSA or use the dosing table below. Note that the mg/kg dosage decreases as body weight increases.

Table 1. IM dose volume based on body weight
Dog body weight |  | Dose volume
lbs | kg | mL
4.4 to 7 | 2 to 3 | 0.3
7.1 to 9 | 3.1 to 4 | 0.4
9.1 to 11 | 4.1 to 5 | 0.6
11.1 to 22 | 5.1 to 10 | 0.8
22.1 to 29 | 10.1 to 13 | 1.0
29.1 to 33 | 13.1 to 15 | 1.2
33.1 to 44 | 15.1 to 20 | 1.4
44.1 to 55 | 20.1 to 25 | 1.6
55.1 to 66 | 25.1 to 30 | 1.8
66.1 to 73 | 30.1 to 33 | 2.0
73.1 to 81 | 33.1 to 37 | 2.2
81.1 to 99 | 37.1 to 45 | 2.4
99.1 to 110 | 45.1 to 50 | 2.6
110.1 to 121 | 50.1 to 55 | 2.8
121.1 to 132 | 55.1 to 60 | 3.0
132.1 to 143 | 60.1 to 65 | 3.2
143.1 to 154 | 65.1 to 70 | 3.4
154.1 to 176 | 70.1 to 80 | 3.6
>176 | >80 | 3.8

After administration of Zenalpha, the dog should be allowed to rest quietly until evidence of sedation has occurred (5-15 minutes). The average duration of sedation is 38 minutes. As with all alpha2-adrenoceptor agonists, onset of sedation may be delayed or may be inadequate in some dogs.

Reversal of Zenalpha: Administration of IM atipamezole hydrochloride at the approved dose to reverse IM medetomidine hydrochloride results in reversal of the sedative and cardiovascular effects of Zenalpha. Reversal of sedation occurs within 5-10 minutes after administration of atipamezole hydrochloride.

CONTRAINDICATIONS:

Do not use Zenalpha in dogs with cardiac disease, respiratory disorders, shock, severe debilitation, that have hypoglycemia or are at risk of developing hypoglycemia, or are stressed due to extreme heat, cold or fatigue.

Zenalpha is contraindicated in dogs with a known sensitivity to medetomidine or vatinoxan.

WARNINGS:

Human User Safety Warnings

Not for use in humans. Keep this and all medications out of reach of children and pets.

Avoid skin, eye or mucosal contact. Use caution while handling and using filled syringes. Absorption of the active ingredients is possible following exposure via the skin, eye or mucosa. In case of accidental eye exposure, flush eyes with water for 15 minutes, remove contact lenses then continue to flush. In case of accidental skin exposure, wash with soap and water and remove contaminated clothing. If symptoms occur, seek the advice of a physician.

In case of accidental oral intake or self-injection, seek medical advice immediately and show the package insert to the physician. DO NOT DRIVE as sedation, loss of consciousness, and changes in blood pressure may occur.

Persons with cardiovascular disease (for example, hypertension or ischemic heart disease) should take special precautions to avoid any exposure to this product.

Pregnant women should exercise special caution to avoid exposure. Uterine contractions and decreased fetal blood pressure may occur after accidental systemic exposure.

Persons with known hypersensitivity to any of the ingredients should avoid contact with Zenalpha.

Caution should be exercised when handling sedated animals. Handling or any other sudden stimuli, including noise, may cause a defense reaction in an animal that appears to be heavily sedated.

Note to physician: Zenalpha contains medetomidine, an alpha2-adrenoceptor agonist, in combination with vatinoxan, a peripherally selective alpha2-adrenoceptor antagonist. Symptoms after absorption or accidental self-injection may include dose-dependent sedation, respiratory depression, bradycardia, tachycardia, and hypotension.

Animal Safety Warnings

Zenalpha should not be administered in the presence of pre-existing hypotension, hypoxia or bradycardia. Due to the pronounced cardiovascular effects of alpha2-adrenoceptor agonists, only clinically healthy dogs (American Society of Anesthesiologists [ASA] classes I and II) should be administered Zenalpha. Dogs should be monitored frequently for cardiovascular function and body temperature during sedation.

Zenalpha is not intended for use in cats. The use of Zenalpha in cats has been associated with hypotension.

PRECAUTIONS:

Dogs should be monitored frequently during sedation for changes in heart rate, blood pressure, respiratory rate and body temperature. Tachycardia may occur in some dogs after recovery from sedation.

In the event of hypoxia or apnea, supplemental oxygen should be administered.

Following administration of Zenalpha, a decrease in body temperature may occur and an external heat source may be needed to maintain body temperature. Hypothermia may persist longer than sedation and analgesia.

The analgesic effect of Zenalpha will not last longer than the sedative effects. Additional analgesic(s) should be administered as needed (see Effectiveness).

Nervous, excited or agitated dogs with high levels of endogenous catecholamines may exhibit a reduced pharmacological response to Zenalpha (ineffectiveness). The onset of sedative/analgesic effects could be slowed, or the depth and duration of effects could be diminished or nonexistent. Therefore, allow the dog to rest quietly for 10 to 15 minutes after injection.

With the alpha2-adrenoceptor agonist drug class, including Zenalpha, the potential for isolated cases of hypersensitivity, including paradoxical response (excitation) exists.

Repeat dosing with Zenalpha has not been evaluated.

Zenalpha has only been evaluated in fasted dogs; therefore, the effects on fed dogs (for example occurrence of vomiting) has not been characterized.

The concurrent use of anticholinergic medications and Zenalpha has not been evaluated.

Zenalpha may decrease serum glucose in healthy dogs and this effect may persist longer than sedation (see Animal Safety).

The safe use of Zenalpha in dogs with hepatic or renal impairment has not been evaluated.

The safe use of Zenalpha has not been evaluated in dogs younger than 4.5 months old.

The safe use of Zenalpha has not been evaluated in dogs that are pregnant, lactating, or intended for breeding.

ADVERSE REACTIONS:

In the field study safety evaluation, 110 dogs received Zenalpha and 113 dogs received dexmedetomidine (control group) for sedation. Dogs ranged in age from 5 months to 14.5 years, weighed 5.1 to 154 lbs, and represented purebreds and breed mixes.

Table 2. Adverse reactions during the field study
Adverse Reaction | Zenalpha (N = 110) n (%) | Dexmedetomidine (N = 113) n (%)
Diarrhea | 4 (3.6) | 0 (0)
Muscle tremor | 2 (1.8) | 0 (0)
Signs of colitis | 2 (1.8) | 0 (0)
Hypothermia [Hypothermia that necessitated use of an external heat source] | 1 (0.9) | 13 (11.5)
Vomiting | 1 (0.9) | 6 (5.3)
Involuntary defecation | 1 (0.9) | 0 (0)
Nausea | 1 (0.9) | 0 (0)
Tachycardia, transient | 1 (0.9) | 0 (0)
Prolonged sedation | 0 (0) | 3 (2.7)
Urinary incontinence | 0 (0) | 2 (1.8)
Retching | 0 (0) | 1 (0.9)
Apnea | 0 (0) | 1 (0.9)
Bradycardia | 0 (0) | 1 (0.9)
Hyperthermia | 0 (0) | 1 (0.9)

Field Study Safety

Decreased body temperature occurred within 30 minutes after administration for some dogs in both treatment groups and lasted up to 2 hours in the Zenalpha group and 2-6 hours in the control group. There were 57/110 dogs (51.8%) in the Zenalpha group and 77/113 dogs (68.1%) in the control group that had a body temperature ≤99 °F. The respiratory rates decreased in both groups within 5 minutes post dose compared to baseline. The group mean respiratory rate in the Zenalpha group decreased earlier and recovered faster than the control group. Thirty-nine dogs out of 110 (35.4%) in the Zenalpha group and 33/113 dogs (29.2%) in the control group had respiratory rates < 10 breaths per minute (bpm) during the study. The group mean respiratory rate in the Zenalpha group was lowest at 30 minutes post-treatment (14 bpm) and in the control group was lowest at 90 minutes post-treatment (15.5 bpm). Mucous membrane color and capillary refill time were normal for all dogs at all timepoints during the study.

CONTACT INFORMATION:

To report suspected adverse reactions, for technical assistance, or to obtain a copy of the Safety Data Sheet (SDS), call Dechra at (866) 933-2472. For additional information about adverse drug experience reporting for animal drugs, contact FDA at 1-888-FDA-VETS or www.fda.gov/reportanimalae.

CLINICAL PHARMACOLOGY:

Medetomidine is a potent non-narcotic alpha2-adrenoceptor agonist which produces sedation and analgesia. These effects are dose dependent in depth and duration. Medetomidine is a racemic mixture containing the active enantiomer dexmedetomidine. Within the central nervous system, sympathetic neurotransmission is inhibited and the level of consciousness decreases. Respiratory rate and body temperature can also decrease. In the peripheral vasculature, medetomidine stimulates alpha2-adrenoceptors within vascular smooth muscle which induces vasoconstriction and hypertension which consequently decreases the heart rate and cardiac output. Dexmedetomidine also induces a number of other alpha2-adrenoceptor mediated effects, which include piloerection, depression of motor and secretory functions of the gastrointestinal tract, diuresis and hyperglycemia.

Vatinoxan is a peripherally selective alpha2-adrenoceptor antagonist which lacks activity in the central nervous system. By limiting its effects to peripheral organ systems, vatinoxan will prevent or attenuate the cardiovascular and other effects of dexmedetomidine outside the central nervous system when administered simultaneously with the alpha2-adrenoceptor agonist. The central effects of dexmedetomidine remain unaltered, although vatinoxan will reduce the duration of sedation and analgesia induced by dexmedetomidine, predominantly by increasing the clearance of the latter via improving the cardiovascular function.

No pharmacokinetic assessment was performed on Zenalpha [medetomidine (1 mg/m^2) + vatinoxan (20 mg/m^2)]. However, after IM administration of a pilot formulation of medetomidine (1 mg/m^2) + vatinoxan (30 mg/m^2), both medetomidine and vatinoxan were rapidly and highly absorbed from the injection site. Maximal plasma concentration was reached at 12.6 ± 4.7 (mean ± standard deviation) minutes and 17.5 ± 7.4 minutes for dexmedetomidine (the active enantiomer of medetomidine) and vatinoxan, respectively. Vatinoxan increased the volume of distribution and the clearance of dexmedetomidine. Thus, the clearance of dexmedetomidine was increased two-fold when given in combination with vatinoxan. The same phenomena were also observed with intravenous administration.

Medetomidine plasma protein binding is high (85-90%). Medetomidine is mainly oxidized in the liver, a smaller amount undergoes methylation in the kidneys, and excretion is mainly via urine. Vatinoxan plasma protein binding is approximately 70%. Low levels are detectable in the central nervous system. Only a small amount (<5%) of vatinoxan dose has been found to be excreted via the urine.

EFFECTIVENESS:

A prospective, randomized, masked, multi-center study was conducted at six veterinary clinics to evaluate the effectiveness of Zenalpha to provide sedation and analgesia for non-painful or mildly painful, non-invasive procedures and examinations in client-owned dogs. Effectiveness was evaluated in 208 of the 223 enrolled dogs (109 in the Zenalpha group and 99 in the control group). Dogs ranged in age from 5 months to 14.5 years, weighed 5.1 to 154 lbs (2.3-70 kg) and represented purebreds and breed mixes. Dogs received one IM injection of Zenalpha at 1 mg/m^2 medetomidine and 20 mg/m^2 vatinoxan, or dexmedetomidine at 0.5 mg/m^2 (control group) to produce sedation prior to conduct of the examination or procedure. Procedures included: radiographic examination or diagnostic imaging, ear examination and treatment, eye examination and treatment, anal sac treatment, dermatological examination and procedures, dental examination, dental biopsy, dental minor extraction, fine needle aspiration/superficial biopsy, minor surgery to remove dermal masses, drain seroma or abscess, nail trimming, coat grooming, venous blood draw and intravenous catheter placement. Many dogs underwent more than one procedure while sedated.

Effectiveness of Zenalpha was based on: 1) the ability to complete the planned examination or procedure while the dog was sedated, and 2) demonstration of less severe cardiovascular adverse effects (determined by heart rate) compared to the control group. Respiratory rate, body temperature, analgesia, and adverse reactions were evaluated as secondary variables for the safety assessment (see Adverse Reactions). Dogs were evaluated at 5, 15, 30, 60, and 90 minutes and 2, 3, 4, 5 and 6 hours post-treatment. The success rate for ability to complete the procedure was 94.5% (103/109) in the Zenalpha group and 90.9% (90/99) in the control group. The Zenalpha group mean heart rate remained within the normal range (60-140 bpm), while the control group mean heart rate was below normal from 15-180 minutes post-treatment. The mean heart rate in the Zenalpha group was lowest at 15 minutes (64 bpm) and the mean heart rate in the control group was lowest at 90 minutes (45 bpm). There were 9 dogs (8.3%) in the Zenalpha group and 54 dogs (52.4%) in the control group that had heart rates <40 beats per minute (bpm) during sedation. Zenalpha met the criteria for success because it was not inferior to the control product for sedation and completion of the procedure and provided a decrease in the occurrence of bradycardia.

Dogs in the Zenalpha group typically had a shorter time to onset of sedation and shorter duration of sedation compared to the control group. The mean time to onset of sedation was 14 minutes in the Zenalpha group and 18 minutes in the control group. The mean duration of sedation in the Zenalpha group was 38 minutes (maximum of 90 min.) and in the control group was 90 minutes (maximum 5 hrs. 28 min.). The analgesic effects in the Zenalpha and the control groups were similar, and both waned with the loss of sedation.

The results of the field study demonstrated that Zenalpha is safe and effective, and provides sedation and analgesia needed to perform common non-painful or mildly painful veterinary examinations and procedures. Dogs treated with Zenalpha had a shorter time to onset of sedation, shorter duration of sedation (recovered quicker), and less cardiovascular and respiratory depression and adverse reactions compared to dogs in the control group.

ANIMAL SAFETY:

In a 4-day laboratory study using final market formulation, 32 healthy Beagle dogs (4 dogs/sex/group) aged 4.5 - 6.5 months were administered saline control, 1/20 medetomidine/vatinoxan, 3/60 medetomidine/vatinoxan, or 5/100 medetomidine/vatinoxan mg/m^2 Body Surface Area (BSA) by intravenous injection. These Zenalpha doses correspond to 1, 3, or 5X the recommended intramuscular dose. The administration of Zenalpha resulted in sedation, hypotension, hypothermia, and initially sinus bradycardia followed later by sinus tachycardia as the dogs recovered from sedation. Generally, dogs were provided supplemental heat support starting at 1 or 2 hours post-dose and continuing through 4 hours post-dose. Dogs recovered from sedation within 4 hours for the 1X group and 4-8 hours for the 3 and 5X groups. Physiologic variables returned to baseline within 8 hours post-dose in all dose groups. Bloodwork was evaluated 3-4 hours post-dose. Two dogs in the 5X group had decreased blood glucose on post-dose bloodwork. One dog in the 1X group and one dog in the 3X group had decreased potassium on post-dose bloodwork. Clinical observations included mucoid, soft, or watery feces and observations of salivation, trembling, tremors, vocalization, defecation or vomiting after dosing, injected sclera, struggling after dosing, and skin cool to touch. There were no Zenalpha-related effects on moribundity, body weight, ophthalmological examinations, mucous membrane color, capillary refill time, gross pathology observations, organ weights, or histopathological findings.

STORAGE INFORMATION:

Store below 77°F (25°C).

In use shelf life: 3 months at 77°F (25°C).

Protect from freezing and store in outer carton to protect from light.

HOW SUPPLIED:

Zenalpha is supplied in 10 mL multi-dose glass vials. Each mL contains 0.5 mg medetomidine hydrochloride and 10 mg vatinoxan hydrochloride.

NDC 17033-090-05

Approved by FDA under NADA # 141-551

Manufactured for:
Dechra Veterinary Products
7015 College Boulevard, Suite 525
Overland Park, KS 66211 USA

Manufactured in Sweden.

US Patent No(s). 10,058,538 and 9,409,919 by Vetcare Oy.

Zenalpha is a registered trademark of Dechra Limited.
Rev. September 2022

2006825

PRINCIPAL DISPLAY PANEL - 10 mL Vial Carton

Zenalpha®
(medetomidine and vatinoxan hydrochlorides injection)
0.5 mg/mL and 10 mg/mL
For intramuscular injection in dogs only
Sedative, Analgesic

Caution: Federal law restricts this drug to use by or on the order of a licensed veterinarian.

Approved by FDA under
NADA # 141-551

10 mL
Dechra